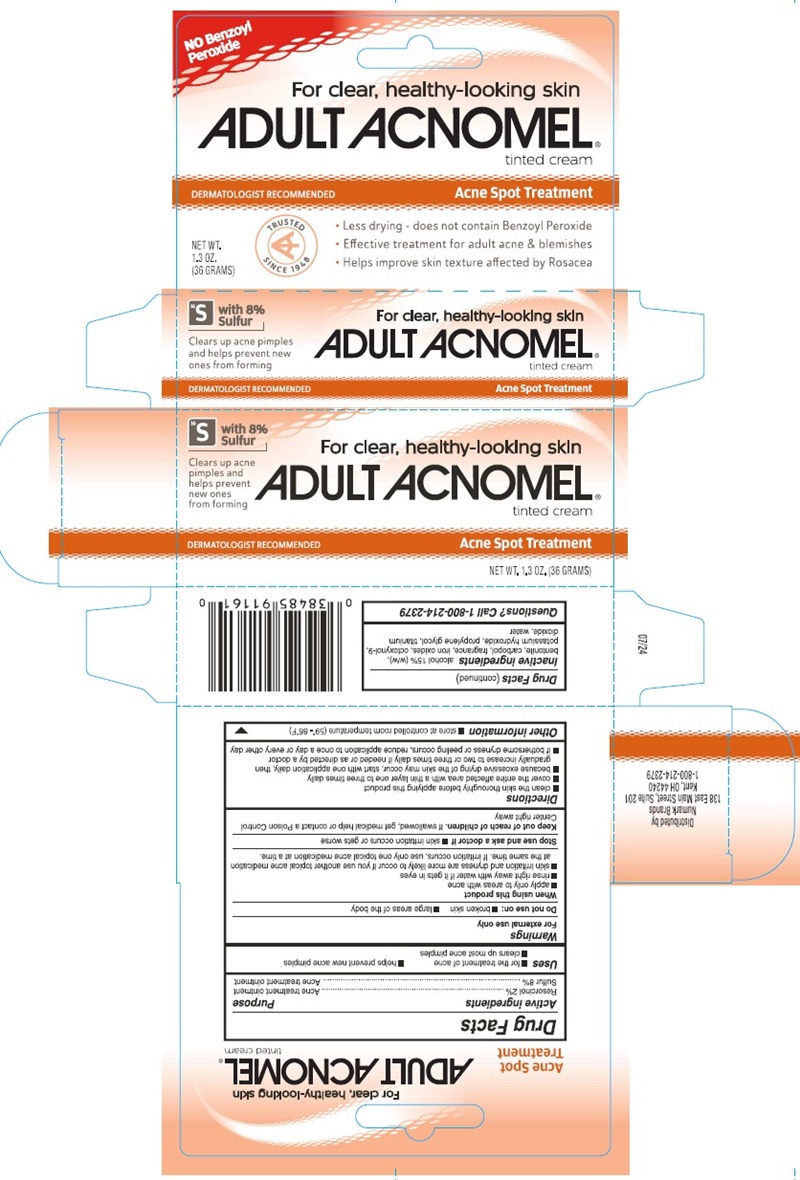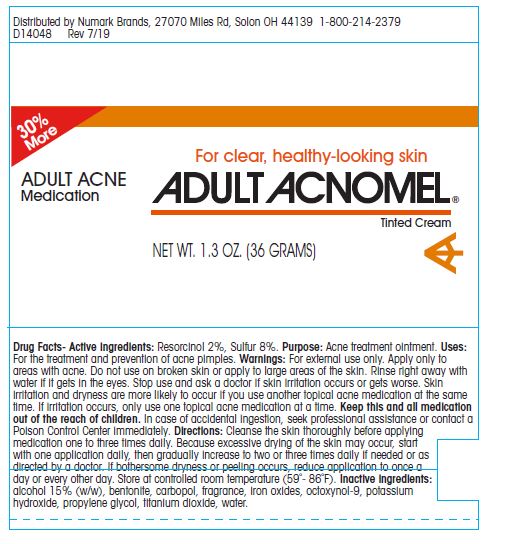 DRUG LABEL: Adult Acnomel
NDC: 69846-911 | Form: CREAM
Manufacturer: NUMARK BRANDS, INC
Category: otc | Type: HUMAN OTC DRUG LABEL
Date: 20251203

ACTIVE INGREDIENTS: RESORCINOL 20 mg/1 g; SULFUR 80 mg/1 g
INACTIVE INGREDIENTS: ALCOHOL; BENTONITE; CARBOMER HOMOPOLYMER TYPE C (ALLYL PENTAERYTHRITOL CROSSLINKED); FERRIC OXIDE RED; OCTOXYNOL-9; POTASSIUM HYDROXIDE; PROPYLENE GLYCOL; TITANIUM DIOXIDE; WATER

Drug Facts

Active Ingredients

Resorcinol 2%
Sulfur 8%

Purpose

Acne treatment ointment

Uses

- for the treatment of acne
- helps prevent new acne pimples
- clears up most acne pimples

Warnings

For external use only

Do not use on:

- broken skin
- large areas of the body

When using this product

- apply only to areas with acne
- rinse right away with water if it gets in eyes
- skin irritation and dryness are more likely to occur if you use another topical acne medication at the same time. If irritation occurs, use only one topical acne medication at a time.

Stop use and ask a doctor if

- skin irritation occurs or gets worse

Keep out of reach of children

If swallowed, get medical help or contact a Poison Control Center right away

Directions

- clean the skin thoroughly before applying this product
- cover the entire affected area with a thin layer one to three times daily
- because excessive drying of the skin may occur, start with one application daily, then gradually increase to two or three times daily if needed or as directed by a doctor
- if bothersome dryness or peeling occurs, reduce application to once a day or every other day

Other information

- store at controlled room temperature (59° - 86° F)

Inactive ingredients

alcohol 15% (w/w), bentonite, carbopol, fragrance, iron oxides, octoxynol-9, potassium hydroxide, propylene glycol, titanium dioxide, water

Questions?

Call 1-800-331-0221

PRINCIPAL DISPLAY PANEL

NO Benzoyl
Peroxide
For clear, healthy-looking skin
ADULT ACNOMEL ®
Tinted Cream
DERMATOLOGIST RECOMMENDED
Acne Spot Treatment
NET WT.
1.3 OZ.
(36 GRAMS)
TRUSTED
SINCE 1948
• Less drying- does not contain Benzoyl Peroxide
• Effective treatment for adult acne & blemishes
• Helps improve skin texture affected by Rosacea
with 8%
Sulfer
Clears up acne pimples
and helps prevent new
ones from forming
Distributed by:
Numark Brands
138 East Main St, Suite 201
Kent, OH 44240
1-800-214-2379
07/24

30% More
ADULT ACNE
Medication
For clear, healthy-looking skin
ADULT ACNOMEL©
Tinted Cream
NET WT. 1.3 OZ. (36 GRAMS)
Distributed by Numark Brands, 27070 Miles Rd, Solon OH 44139 1-800-214-2379
D14048 Rev 7/19